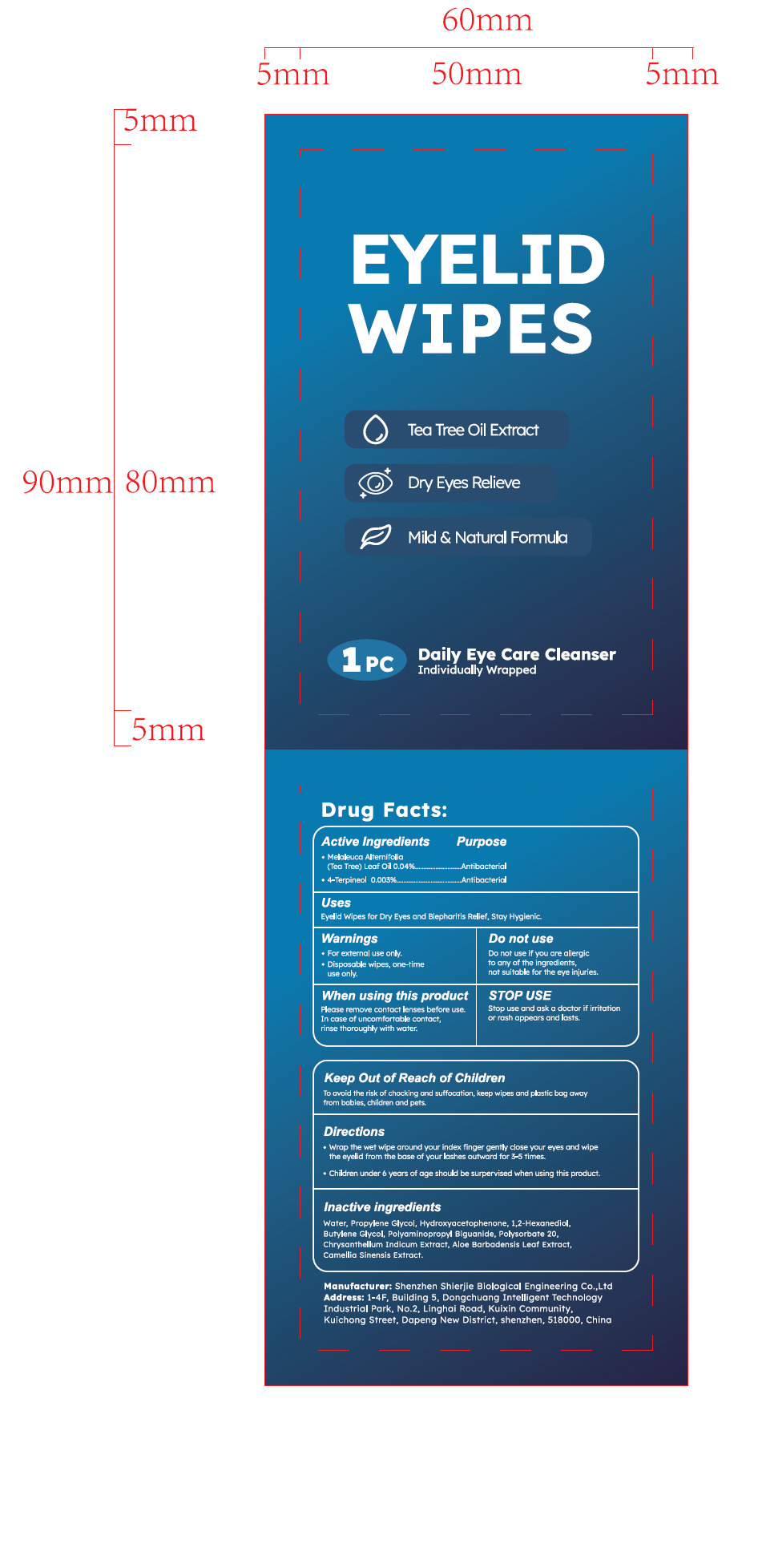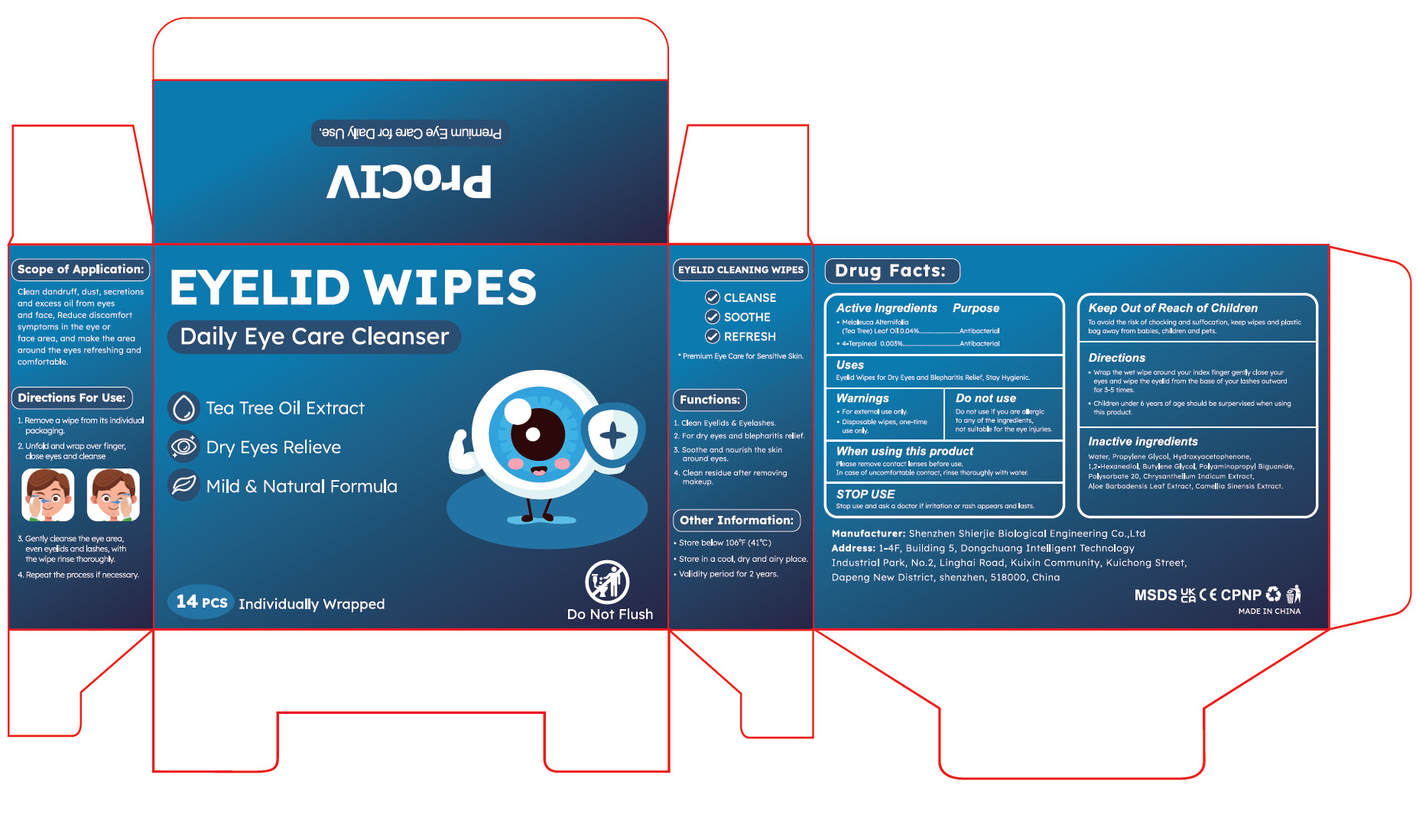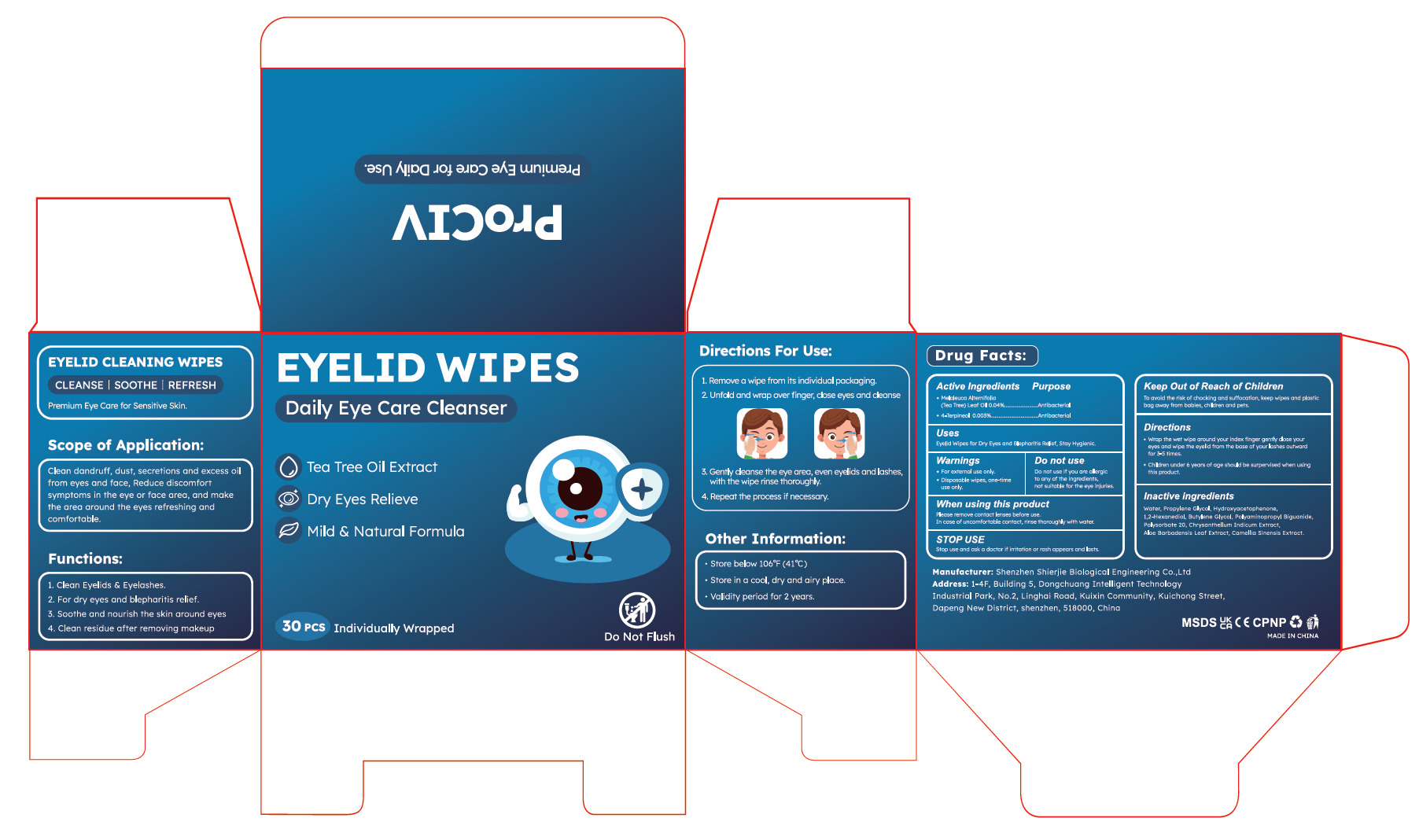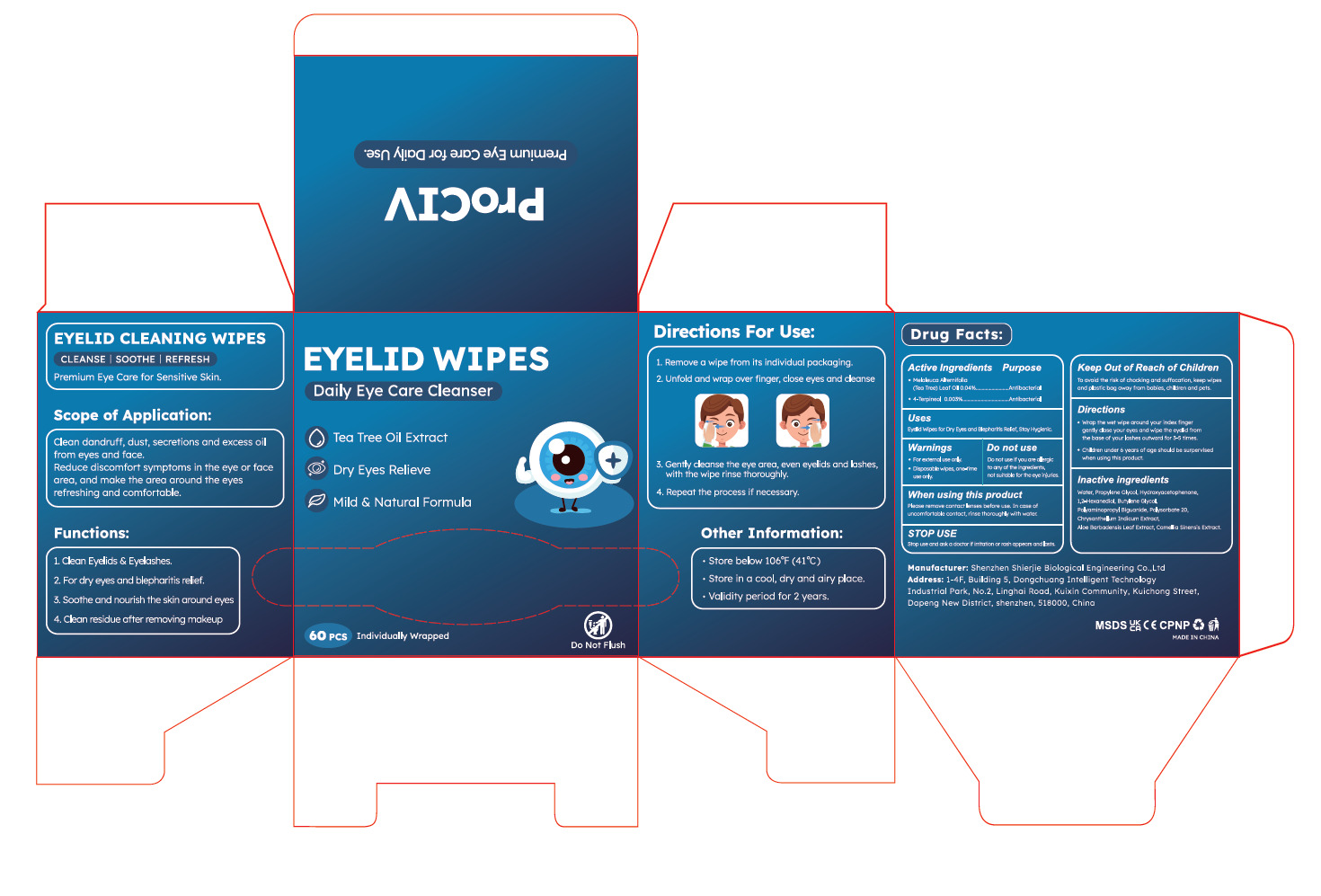 DRUG LABEL: EYELID WIPES
NDC: 43116-043 | Form: CLOTH
Manufacturer: Shenzhen Shierjie Biological Engineering Co., LTD
Category: otc | Type: HUMAN OTC DRUG LABEL
Date: 20250613

ACTIVE INGREDIENTS: MELALEUCA ALTERNIFOLIA (TEA TREE) LEAF OIL 0.04 U/100 U; 4-TERPINEOL 0.003 U/100 U
INACTIVE INGREDIENTS: PROPYLENE GLYCOL; 1,2-HEXANEDIOL; BUTYLENE GLYCOL; ALOE BARBADENSIS LEAF; WATER; POLYSORBATE 20; CHRYSANTHELLUM INDICUM TOP; HYDROXYACETOPHENONE; CAMELLIA SINENSIS LEAF; POLYAMINOPROPYL BIGUANIDE

43116-043

Active Ingredient

Melaleuca Alternifolia(Tea Tree)Leaf Oil 0.04%

4-Terpineol 0.003%

Purpose

Antibacterial

Use

Eyelid Wipes for Dry Eyes and Blepharitis Relief, Stay Hygienic.

Warnings

●For external use only.
●Disposable wipes, one-time use only.

Do not use if you are allergic to any of the ingredients, not suitable for the eye injuries.

When Using

Please remove contact lenses before use. In case of uncomfortable contact, rinse thoroughly with water.

Stop Use

Stop use and ask a doctor if irritation or rash appears and lasts.

Keep Oot Of Reach Of Children

To avoid the risk of chocking and suffocation, keep wipes and plastic bag away
from babies, children and pets.

Directions

●Wrap the wet wipe around your index finger gently close your eyes and wipe
the eyelid from the base of your lashes outward for 3-5 times.
●Children under 6 years of age should be surpervised when using this product.

Other information

●Store below 106°F (41°C)
●Store in a cool, dry and airy place.
●Validity period for 2 years.

Inactive ingredients

Water, Propylene Glycol, Hydroxyacetophenone, 1,2-Hexanediol,
Butylene Glycol, Polyaminopropyl Biguanide, Polysorbate 20,
Chrysanthellum Indicum Extract, Aloe Barbadensis Leaf Extract,
Camellia Sinensis Extract.